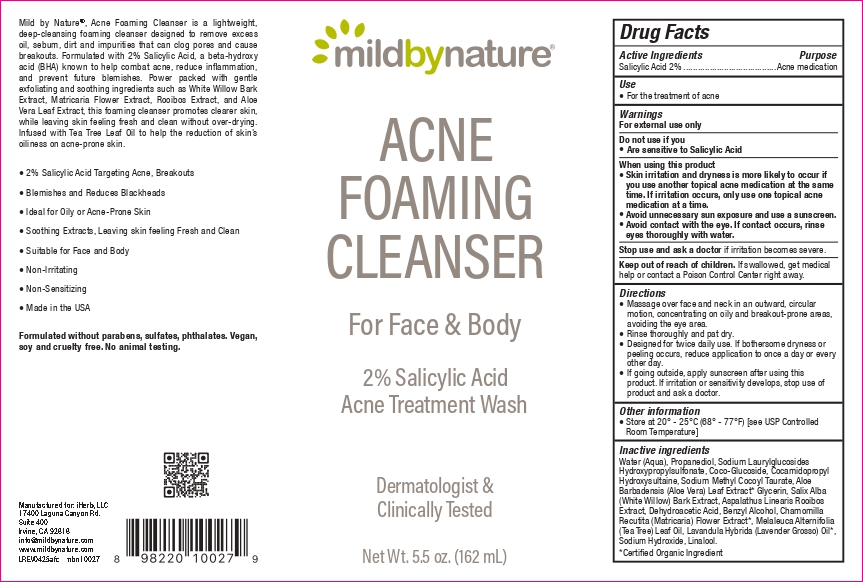 DRUG LABEL: Mild By Nature ACNE FOAMING CLEANSER
NDC: 82287-0003 | Form: LIQUID
Manufacturer: IHerb, LLC
Category: otc | Type: HUMAN OTC DRUG LABEL
Date: 20251103

ACTIVE INGREDIENTS: SALICYLIC ACID 20 mg/1 mL
INACTIVE INGREDIENTS: WATER; MELALEUCA ALTERNIFOLIA (TEA TREE) LEAF OIL; LAVANDULA HYBRIDA OIL; DEHYDROACETIC ACID; ALOE BARBADENSIS LEAF JUICE; SODIUM LAURYLGLUCOSIDES HYDROXYPROPYLSULFONATE; SODIUM METHYL COCOYL TAURATE; BENZYL ALCOHOL; MATRICARIA CHAMOMILLA FLOWERING TOP; ASPALATHUS LINEARIS LEAF; LINALOOL; PROPANEDIOL; SODIUM HYDROXIDE; COCAMIDOPROPYL HYDROXYSULTAINE; GLYCERIN; COCO GLUCOSIDE; SALIX ALBA BARK

HEALTH CLAIM

Mild by Nature®, Acne Foaming Cleanser is a lightweight,
deep-cleansing foaming cleanser designed to remove excess
oil, sebum, dirt and impurities that can clog pores and cause
breakouts. Formulated with 2% Salicylic Acid, a beta-hydroxy
acid (BHA) known to help combat acne, reduce inflammation,
and prevent future blemishes. Power packed with gentle
exfoliating and soothing ingredients such as White Willow Bark
Extract, Matricaria Flower Extract, Rooibos Extract, and Aloe
Vera Leaf Extract, this foaming cleanser promotes clearer skin,
while leaving skin feeling fresh and clean without over-drying.
Infused with Tea Tree Leaf Oil to help the reduction of skin’s
oiliness on acne-prone skin.
• 2% Salicylic Acid Targeting Acne, Breakouts
• Blemishes and Reduces Blackheads
• Ideal for Oily or Acne-Prone Skin
• Soothing Extracts, Leaving skin feeling Fresh and Clean
• Suitable for Face and Body
• Non-Irritating
• Non-Sensitizing
• Made in the USA
Formulated without parabens, sulfates, phthalates. Vegan,
soy and cruelty free. No animal testing.

DESCRIPTION

mbn10027
Manufactured for: iHerb, LLC
17400 Laguna Canyon Rd.
Suite 400
Irvine, CA 92618
info@mildbynature.com
www.mildbynature.com

Active Ingredients Purpose

Salicylic acid 2.0%....................Acne medication

Use
• For the treatment of acne.

Do not use if you
• Are sensitive to Salicylic Acid.

Keep out of reach of children, if swallowed, get medical help or contact a Poison Control Center right away

When using this product
• Skin irritation and dryness is more likely to occur if
you use another topical acne medication at the same
time. If irritation occurs, only use one topical acne
medication at a time.
• Avoid unnecessary sun exposure and use a sunscreen.
• Avoid contact with the eye. If contact occurs, rinse
eyes thoroughly with water.

Stop use and ask a doctor if irritation becomes severe.

Other information
• Store at 20° - 25°C (68° - 77°F) [see USP Controlled Room Temperature].

Inactive ingredients
Water (Aqua), Propanediol, Sodium Laurylglucosides
Hydroxypropylsulfonate, Coco-Glucoside, Cocamidopropyl
Hydroxysultaine, Sodium Methyl Cocoyl Taurate, Aloe
Barbadensis (Aloe Vera) Leaf Extract, Glycerin, Salix Alba
(White Willow) Bark Extract, Aspalathus Linearis Rooibos
Extract, Dehydroacetic Acid, Benzyl Alcohol, Chamomilla
Recutita (Matricaria) Flower Extract, Melaleuca Alternifolia
(Tea Tree) Leaf Oil, Lavandula Hybrida (Lavender Grosso) Oil,
Sodium Hydroxide, Linalool.

Warnings For external use only

Directions
• Massage over face and neck in an outward, circular
motion, concentrating on oily and breakout-prone areas,
avoiding the eye area.
• Rinse thoroughly and pat dry.
• Designed for twice daily use. If bothersome dryness or
peeling occurs, reduce application to once a day or every
other day.
• If going outside, apply sunscreen after using this
product. If irritation or sensitivity develops, stop use of
product and ask a doctor.

Directions
• Massage over face and neck in an outward, circular
motion, concentrating on oily and breakout-prone areas,
avoiding the eye area.
• Rinse thoroughly and pat dry.
• Designed for twice daily use. If bothersome dryness or
peeling occurs, reduce application to once a day or every
other day.
• If going outside, apply sunscreen after using this
product. If irritation or sensitivity develops, stop use of
product and ask a doctor.

PACKAGE LABEL

milkd by nature

ACNE
FOAMING
CLEANSER

For Face & Body

2% Salicylic Acid
Acne Treatment Wash

Dermatologist &
Clinically Tested